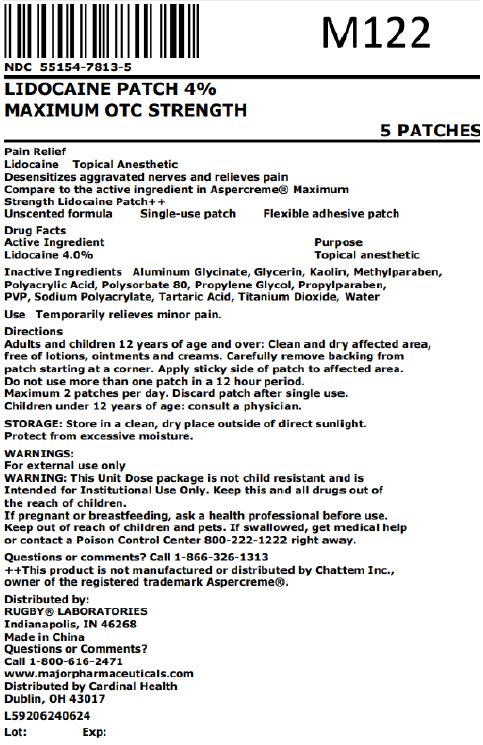 DRUG LABEL: Lidocaine 4%
NDC: 55154-7813 | Form: PATCH
Manufacturer: Cardinal Health 107, LLC
Category: otc | Type: HUMAN OTC DRUG LABEL
Date: 20251020

ACTIVE INGREDIENTS: LIDOCAINE 4 g/100 g
INACTIVE INGREDIENTS: DIHYDROXYALUMINUM AMINOACETATE ANHYDROUS; GLYCERIN; KAOLIN; METHYLPARABEN; POLYACRYLIC ACID (300000 MW); POLYSORBATE 80; PROPYLENE GLYCOL; PROPYLPARABEN; POVIDONE, UNSPECIFIED; SODIUM POLYACRYLATE (2500000 MW); TARTARIC ACID; TITANIUM DIOXIDE; WATER

Rugby PAIN RELIEF PATCHES

Active Ingredient

Lidocaine 4.0%

Purpose

Topical anesthetic

Use

Temporarily es minor pain.

Warnings

For external use only.

Do not use

■ More than one patch on your body at a time

■ On cut, irritated or swollen skin

■ On puncture wounds

■ For more than one week without consulting a doctor

■ If you are allergic to any active or inactive ingredients

■ If pouch is damaged or opened.

When using this product

■ Use only as directed

■ Read and follow all directions and warnings on this carton

■ Do not allow contact with the eyes

■ Do not use at the same time as other topical analgesics

■ Do not bandage tightly or apply local heat (such as heating pads) to the area of use

■ Do not microwave

■ Dispose of used patch in manner that always keeps product away from children and pets. Used patches still contain the drug product that can produce serious adverse effects if a child or pet chews or ingests this patch.

Stop use and consult a doctor

■ Condition worsens

■ Redness is present

■ Irritation develops

■ Symptoms persist for more than 7 days or clear up and occur again within a few days

■ You experience signs of skin injury, such as pain, swelling or blistering where the product was applied.

If pregnant or breastfeeding

ask a health professional before use

Keep out of reach of children and pets

If swallowed, get medical help or contact a Poison Control Center 800-222-1222 right away.

Directions

Directions Adults and children 12 years of age and over: Clean and dry affected area, free of lotions, ointments and creams. Carefully remove backing from patch starting at a corner. Apply sticky side of patch to affected area. Do not use more than one patch in a 12 hour period. Maximum 2 patches per day. Discard patch after single use. Children under 12 years of age: consult a physician.

Other safety information

Store in a clean, dry place outside of direct sunlight. Protect from excessive moisture.

Inactive Ingredients

aluminum glycinate, glycerin, kaolin, methylparaben, polyacrylic acid, polysorbate 80, propylene glycol, propylparaben, PVP, sodium polyacrylate, tartaric acid, titanium dioxide, water

Questions or comments?

Call 1-866-326-1313

.

*This product is not manufactured or distributed by Chattem Inc., owner of the registered trademark Aspercream®.

Distributed by:

RUGBY® LABORATORIES

Undianapolis, IN 46268

Made in China

Questions or comments?

Call 1-800-616-2471

www.majorpharmaceuticals.com

Distributed By:

Cardinal Health

Dublin, OH 43017

L59206240624

Rev. 12/23 | R-153 | Re-order No. 371082

Principal Display Panel

NDC 55154-7813-5

LIDOCAINE PATCH 4%

MAXIMUM OTC STRENGTH

5 PATCHES